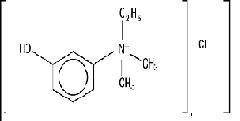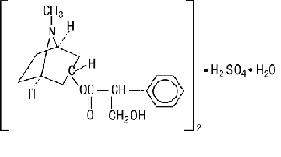 DRUG LABEL: Unknown
Manufacturer: Baxter Healthcare Corporation
Category: prescription | Type: HUMAN PRESCRIPTION DRUG LABELING
Date: 20060309

ENLON-PLUS (edrophonium chloride, USP and atropine sulfate, USP) Injection
Rx only

DESCRIPTION

ENLON-PLUS (edrophonium chloride, USP and atropine sulfate, USP) Injection, for intravenous use, is a sterile, nonpyrogenic, nondepolarizing neuromuscular relaxant antagonist. ENLON-PLUS is a combination drug containing a rapid acting acetylcholinesterase inhibitor, edrophonium chloride, and an anticholinergic, atropine sulfate. Chemically, edrophonium chloride is ethyl (m-hydroxyphenyl) dimethylammonium chloride; its structural formula is:

Molecular Formula: C10H16ClNO

Molecular Weight: 201.70

Chemically, atropine sulfate is: endo-(±)-alpha-(hydroxymethyl)-8-methyl-8-azabicyclo [3.2.1]oct-3-yl benzeneacetate sulfate (2:1) monohydrate. Its structural formula is:

Molecular Formula: (C17H23NO3)2·H2SO4·H2O

Molecular Weight: 694.84

ENLON-PLUS contains in each mL of sterile solution:

5 mL Ampuls: 10 mg edrophonium chloride and 0.14 mg atropine sulfate compounded with 2.0 mg sodium sulfite as a preservative and buffered with sodium citrate and citric acid. The pH range is 4.0-5.0.

15 mL Multidose Vials: 10 mg edrophonium chloride and 0.14 mg atropine sulfate compounded with 2.0 mg sodium sulfite and 4.5 mg phenol as a preservative and buffered with sodium citrate and citric acid. The pH range is 4.0-5.0.

CLINICAL PHARMACOLOGY

Pharmacodynamics

ENLON-PLUS (edrophonium chloride, USP and atropine sulfate, USP) Injection is a combination of an anticholinesterase agent, which antagonizes the action of nondepolarizing neuromuscular blocking drugs, and a parasympatholytic (anticholinergic) drug, which prevents the muscarinic effects caused by inhibition of acetylcholine breakdown by the anticholinesterase. Edrophonium chloride antagonizes the effect of nondepolarizing neuromuscular blocking agents primarily by inhibiting or inactivating acetylcholinesterase. By inactivating the acetylcholinesterase enzyme, acetylcholine is not hydrolyzed as rapidly by acetylcholinesterase and is thereby allowed to accumulate. The greater quantity of acetylcholine reaching the sites of nicotinic cholinergic postjunctional receptors improves transmission of impulses across the myoneural junction. The concomitant, unavoidable accumulation of acetylcholine at the sites of muscarinic cholinergic transmission occurring at the parasympathetic, postganglionic receptors of the autonomic nervous system, may cause bradycardia, bronchoconstriction, increased secretions, and other parasympathomimetic side effects. The magnitude of these muscarinic side effects can be expected to vary from patient to patient depending upon the amount of vagal nerve activity present. Atropine sulfate counteracts these side effects.

Intravenous edrophonium chloride in doses of 0.5 to 1.0 mg/kg promptly antagonizes the effects of nondepolarizing muscle relaxants reaching the maximum antagonism within 1.2 minutes. A plateau of maximal antagonism is sustained for 70 minutes1. Intravenous atropine sulfate has an immediate effect on heart rate which reaches a peak in 2 to 16 minutes and lasts 170 minutes after an average 0.02 mg/kg dose.

Pharmacokinetics

Edrophonium Chloride

Edrophonium chloride given intravenously shows first order elimination in a two compartment open pharmacokinetic model3. Onset of reversal of muscle relaxant induced depression in twitch tension occurs within three minutes. Edrophonium is primarily renally excreted with 67% of the dose appearing in the urine4. Hepatic metabolism and biliary excretion have also been demonstrated in animals4,8. While infants and children have been shown to have a reduced plasma half-life and an increased clearance of edrophonium, doses in children are not significantly different from adults on a mg/kg basis although they are more variable in effect. Conversely, elderly subjects (>75 years old) have a prolonged plasma half-life and a reduced clearance. Studies have shown that in spite of these changes the onset and duration of action is unchanged in these patients.

Table of Pharmacokinetic Values for Edrophonium Chloride

Population | T1/2ß hr±S.D. | VD L/kg±S.D. | Cl mL/kg/min±S.D. | N | Ref.
Adults | 1.8±0.6 | 1.1±0.2 | 9.6±2.7 | 10 | 3
Anephric Patients [No adjustments of edrophonium dosage are required because elimination of non-depolarizing muscle relaxants is similarly decreased.] [Values for anephric patients were calculated using a non-compartmental model.] | 3.4±1.0 | 0.68±0.13 | 2.7±1.4 | 6 | 4
Infants (3 wks-11 mos) | 1.2±0.5 | 1.2±0.2 | 17.8±1.2 | 4 | 5
Children (1-6 yr) | 1.6±0.5 | 1.2±0.7 | 14.2±7.3 | 4 | 5
Adults | [From a study using a different, less sensitive HPLC method and fitting C vs T data to a biexponential curve.] 0.9±0.3 | 1.1±0.6 | 13.3±5 | 5 | 6
Elderly (over 75 yr) | 1.4±0.3 | 0.6±0.1 | 5.1±1 | 5 | 6

T1/2ß= Elimination half-life

VD= Volume of distribution

Cl= Clearance

Atropine Sulfate

Atropine sulfate given intravenously shows first order elimination in a two compartment open model^7. Approximately 57% of a dose of atropine appears in the urine as unchanged drug. Tropine is the primary hepatic metabolite of atropine and it accounts for approximately 30% of the dose^2. Atropine is only 14±9% bound to plasma proteins^7. Atropine clearance in children under 2 years old and in the elderly is decreased in relation to normal healthy adults.

Table of Pharmacokinetic Values for Atropine Sulfate
Population | T1/2ß hr±S.D. | VD L/kg±S.D. | Cl mL/kg/min±S.D. | N | Ref.
Adults | 3.0±0.9 | 1.6±0.4 | 6.8±2.9 | 8 | 7
Children(0.08-10 yrs) | 4.8±3.5 | 2.2±1.5 | 6.4±3.9 | 13 | 7
Elderly [No dose adjustment required because the cardiovascular effect of atropine is diminished in the elderly.] (65-75 yrs) | 10.0±7.3 | 1.8±1.2 | 2.9±1.9 | 10 | 7

T1/2ß = Elimination half-life

VD = Volume of distribution

Cl = Clearance

INDICATIONS AND USAGE

ENLON-PLUS (edrophonium chloride, USP and atropine sulfate, USP) Injection is recommended as a reversal agent or antagonist of nondepolarizing neuromuscular blocking agents. It is not effective against depolarizing neuromuscular blocking agents. It is also useful if used adjunctively in the treatment of respiratory depression caused by curare overdosage.

The appropriateness of the specific fixed ratio of edrophonium and atropine contained in ENLON-PLUS has not been evaluated in myasthenia gravis. Therefore, ENLON-PLUS is not recommended for use in the differential diagnosis of this condition.

CONTRAINDICATIONS

ENLON-PLUS (edrophonium chloride, USP and atropine sulfate, USP) Injection is not to be used in patients with known hypersensitivity to either of the components, or in patients with intestinal or urinary obstruction of mechanical type. Atropine sulfate is contraindicated in the presence of acute glaucoma, adhesions (synechiae) between the iris and lens of the eye, and pyloric stenosis.

WARNINGS

ENLON-PLUS (edrophonium chloride, USP and atropine sulfate, USP) Injection should be used with caution in patients with bronchial asthma or cardiac arrhythmias. Cardiac arrest has been reported to occur in digitalized patients as well as in jaundiced subjects receiving cholinesterase inhibitors. In patients with cardiovascular disease, given anesthesia with narcotic and nitrous oxide without a potent inhalational agent, there is increased risk for clinically significant bradycardia. In patients receiving beta-adrenergic blocking agents there is increased risk for excessive bradycardia from unopposed parasympathetic vagal tone. Such patients should receive atropine sulfate alone prior to ENLON-PLUS. Isolated instances of respiratory arrest have also been reported following the administration of edrophonium chloride. Additional atropine sulfate (1 mg) should be available for immediate use to counteract severe cholinergic reaction which may occur in hypersensitive individuals when ENLON-PLUS is used.

ENLON-PLUS contains sodium sulfite, a sulfite that may cause allergic-type reactions including anaphylactic symptoms and life-threatening or less severe asthmatic episodes in certain susceptible people. The overall prevalence of sulfite sensitivity in the general population is unknown and probably low. Sulfite sensitivity is seen more frequently in asthmatic than in nonasthmatic people.

There is a potential for tissue irritation by extravascular injection.

PRECAUTIONS

General

As with any antagonist of nondepolarizing muscle relaxants, adequate recovery of voluntary respiration and neuromuscular transmission must be obtained prior to the discontinuation of respiratory assistance. Should a patient develop “anticholinesterase insensitivity” for brief or prolonged periods, the patient should be carefully monitored and the dosage of anticholinesterase drugs reduced or withheld until the patient again becomes sensitive to them. Use with caution in patients with prostatic hypertrophy and in debilitated patients with chronic lung disease.

When used in therapeutic doses, atropine can cause dryness of the mouth. This effect is additive when the product is administered with other drugs that can cause dryness of the mouth.

Since atropine sulfate slows gastric emptying and gastrointestinal motility, it may interfere with the absorption of other medications. The effect of atropine on dryness of the mouth may be increased if it is given with other drugs that have anticholinergic action (tricyclic antidepressants, antipsychotics, some antihistamines, and antiparkinsonism drugs).

Drug Interactions

ENLON-PLUS (edrophonium chloride, USP and atropine sulfate, USP) Injection should not be administered prior to the administration of any nondepolarizing muscle relaxants. It should be administered with caution to patients with symptoms of myasthenic weakness who are also on anticholinesterase drugs. Anticholinesterase overdosage (cholinergic crisis) symptoms may mimic underdosage (myasthenic weakness), so the use of this drug may worsen the condition of these patients (see OVERDOSAGE section for treatment).

Narcotic analgesics, except when combined with potent inhaled anesthetics, appear to potentiate the effect of edrophonium on the sinus node and conduction system, increasing both the frequency and duration of bradycardia. In patients with cardiovascular disease, given anesthesia with narcotic and nitrous oxide without a potent inhalational agent, there is increased risk for clinically significant bradycardia. In patients receiving beta-adrenergic blocking agents there is increased risk for excessive bradycardia from unopposed parasympathetic vagal tone. Such patients should receive atropine sulfate alone prior to ENLON-PLUS.

Compared to muscle relaxants with some vagolytic activity, muscle relaxants with no vagolytic effects, i.e. vecuronium, may be associated with a slightly higher incidence of vagotonic effects such as bradycardia and first-degree heart block when reversed with ENLON-PLUS.

Pregnancy Category C

Animal reproduction studies have not been conducted with ENLON-PLUS. It is also not known whether ENLON-PLUS can cause fetal harm when administered to a pregnant woman or can affect reproduction capacity. ENLON-PLUS should be used during pregnancy only if the potential benefit justifies the potential risk to the fetus.

Labor and Delivery

The effect of ENLON-PLUS on the mother and fetus, on the duration of labor or delivery, in the possibility that a forceps delivery or other intervention or resuscitation of the newborn will be necessary, is not known. The effect of the combination drug on the later growth, development and functional maturation of the child is also unknown.

Nursing Mothers

The safety of ENLON-PLUS during lactation in humans has not been established.

Pediatric Use

Safety and effectiveness in pediatric patients have not been established. Pediatric patients may have increased vagal tone. The effect of fixed ratios of edrophonium and atropine on heart rate in such patients has not been evaluated.

Geriatric Use

Clinical studies of ENLON-PLUS did not include sufficient numbers of subjects aged 65 and over to determine whether they respond differently from younger subjects. Other reported clinical experience has not identified differences in responses between the elderly and younger patients. In general, dose selection for an elderly patient should be cautious, usually starting at the low end of the dosing range, reflecting the greater frequency of decreased hepatic, renal, or cardiac function, and of concomitant disease or other drug therapy.

ADVERSE REACTIONS

Cardiovascular

Arrhythmias Frequency >10%: junctional rhythm, bradycardia, tachycardia; Frequency 3-10%: first and second degree A-V block, P Wave changes, atrial premature contractions; Frequency 1-3%: third degree A-V block, ventricular premature contractions; Frequency less than 1%: 3 second R-R interval.

Of the patients who experienced any arrhythmias, 85% had the onset within two minutes, 74% no longer had any arrhythmias after 10 minutes. Arrhythmias related to increased vagal tone, bradycardia, second and third degree heart block respond to treatment with 0.2-0.4 mg of atropine I.V. (Bigeminy or ventricular ectopy may be treated with lidocaine 50 mg I.V.).

Adverse experiences reported for anticholinesterase agents such as edrophonium chloride, but not observed in the 235 patients studied with ENLON-PLUS (edrophonium chloride, USP and atropine sulfate, USP) Injection:

Cardiovascular

Nonspecific EKG changes, fall in cardiac output leading to hypotension;

Respiratory

Increased tracheobronchial secretions, laryngospasm, bronchiolar constriction and respiratory muscle paralysis;

Neurologic

Convulsions, dysarthria, dysphonia, and dysphagia;

Gastrointestinal

Nausea, vomiting, increased peristalsis, increased gastric and intestinal secretions, diarrhea, abdominal cramps;

Musculoskeletal

Weakness and fasciculations;

Miscellaneous

Increased urinary frequency, diaphoresis, increased lacrimation, pupillary constriction, diplopia, and conjunctival hyperemia.

Untoward reactions to atropine sulfate generally are dose-related. Individual tolerance varies greatly but systemic doses of 0.5 to 10 mg are likely to produce the following effects, which were not observed in the 235 patients treated with ENLON-PLUS:

Neurologic

Speech disturbances and restlessness with asthenia;

Dermatologic

Flushed, dry skin, formation of a scarlatiniform rash;

Miscellaneous

Dryness of the nose and mouth, thirst, blurred vision, photophobia, slight mydriasis. Atropine may produce fever through inhibition of heat loss by evaporation.

OVERDOSAGE

Muscarinic symptoms (nausea, vomiting, diarrhea, sweating, increased bronchial and salivary secretions and bradycardia) may appear with overdosage (cholinergic crisis) of ENLON-PLUS (edrophonium chloride, USP and atropine sulfate, USP) Injection, but may be managed by the use of additional atropine sulfate. Obstruction of the airway by bronchial secretions can arise and may be managed with suction (especially if tracheostomy has been performed).

Should edrophonium chloride overdosage occur:

1. Maintain respiratory exchange.
2. Monitor cardiac function.

Appropriate measures should be taken if convulsions occur or shock is present.

Principal manifestations of overdosage (poisoning) with atropine sulfate are delirium, tachycardia and fever. In the treatment of atropine poisoning, respiratory assistance and symptomatic support are indicated. Death is usually due to paralysis of the medullary centers.

In the clinical studies performed with ENLON-PLUS, there were no reported overdoses and therefore no clinical information is available regarding overdosing with ENLON-PLUS.

DOSAGE AND ADMINISTRATION

Dosages of ENLON-PLUS (edrophonium chloride, USP and atropine sulfate, USP) Injection range from 0.05-0.1 mL/kg given slowly over 45 seconds to 1 minute at a point of at least 5% recovery of twitch response to neuromuscular stimulation (95% block). The dosage delivered is 0.5-1.0 mg/kg of edrophonium chloride and 0.007-0.014 mg/kg of atropine sulfate. A total dosage of 1.0 mg/kg of edrophonium chloride should rarely be exceeded. Response should be monitored carefully and assisted or controlled ventilation secured. Satisfactory reversal permits adequate voluntary respiration and neuromuscular transmission (as tested with a peripheral nerve stimulator). Recurarization has not been reported after satisfactory reversal has been attained.

Parenteral drug products should be inspected visually for particulate matter and discoloration prior to administration.

HOW SUPPLIED

ENLON-PLUS (edrophonium chloride, USP and atropine sulfate, USP) Injection should be stored between 15º-26ºC (59º-78ºF).

NDC 10019-180-05 5 mL ampuls, boxes of 10

NDC 10019-195-15 15 mL multidose vials

REFERENCES

1. Cronnelly R, Morris RB, Miller RD: Edrophonium: Duration of action and atropine requirement in humans during halothane anesthesia. Anesthesiology 1982;57:261-266.
2. Hinderling PH, Gundert-Remy U, Schmidlin O, Heinzel G: Integrated pharmacokinetics and pharmacodynamics of atropine in healthy humans. I: Pharmacokinetics; II: Pharmacodynamics. J Pharmaceutical Sci 1985; 74:I-703-710; II-711-717.
3. Morris RB, Cronnelly R, Miller RD, Stanski DR, Fahey MR: Pharmacokinetics of edrophonium and neostigmine when antagonizing d- tubocurarine neuromuscular blockade in man. Anesthesiology 1981;54:399-402.
4. Morris RB, Cronnelly R, Miller RD, Stanski DR, Fahey MR: Pharmacokinetics of edrophonium in anephric and renal transplant patients. Br J Anaesth 1981;53:1311-1313.
5. Fisher DM, Cronnelly R, Sharma M, Miller RD: Clinical pharmacology of edrophonium in infants and children. Anesthesiology 1984; 61:428-433.
6. Silverberg PA, Matteo RS, Ornstein E, Young WL, Diaz J: Pharmacokinetics and pharmacodynamics of edrophonium in the elderly. Anesth Analg 1986;65:S142.
7. Virtanen R, Kanto J, Iisalo E, Iisalo EU, Salo M, Sjovall S: Pharmacokinetic studies on atropine with special reference to age. Acta Anaesthesiol Scand 1982;26:297-300.
8. Back DJ, Calvey TN: Excretion of 14C-edrophonium and its metabolites in bile: role of the liver cell and the peribiliary vascular plexus. Br J Pharmacol., 1972; 44:534.

Baxter and Enlon-Plus are trademarks of Baxter International, Inc.

Manufactured for

Baxter Healthcare Corporation

Deerfield, IL 60015 USA

by: Taylor Pharmaceuticals

Decatur, IL 62525

For Product Inquiry 1 800 ANA DRUG (1-800-262-3784)

MLT-47/1.0